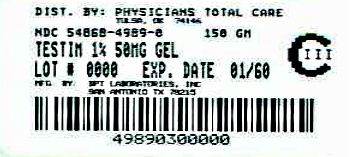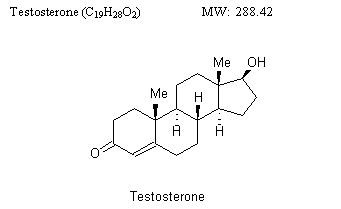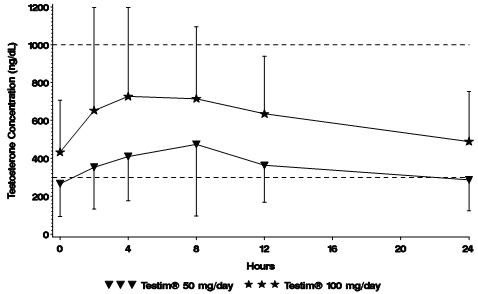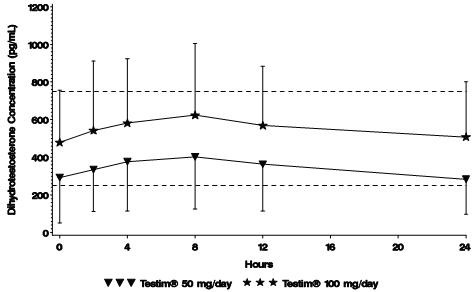 DRUG LABEL: Testim
NDC: 54868-4989 | Form: GEL
Manufacturer: Physicians Total Care, Inc.
Category: prescription | Type: HUMAN PRESCRIPTION DRUG LABEL
Date: 20120419
DEA Schedule: CIII

ACTIVE INGREDIENTS: TESTOSTERONE 50 mg/5 g

Testim® 1% (testosterone gel) CIII

WARNING: SECONDARY EXPOSURE TO TESTOSTERONE

- Virilization has been reported in children who were secondarily exposed to testosterone gel.
- Children should avoid contact with unwashed or unclothed application sites in men using testosterone gel.
- Healthcare providers should advise patients to strictly adhere to recommended instructions for use.

(See WARNINGS, Potential for Secondary Exposure to Testosterone)

DESCRIPTION

Testim® (testosterone gel) is a clear to translucent hydroalcoholic topical gel containing 1% testosterone. Testim® provides continuous transdermal delivery of testosterone for 24 hours, following a single application to intact, clean, dry skin of the shoulders and upper arms.

One 5 g or two 5 g tubes of Testim® contains 50 mg or 100 mg of testosterone, respectively, to be applied daily to the skin’s surface. Approximately 10% of the applied testosterone dose is absorbed across skin of average permeability during a 24-hour period.

The active pharmacological ingredient in Testim® is testosterone.

Testosterone USP is a white to practically white crystalline powder chemically described as 17-β hydroxyandrost-4-en-3-one. Inactive ingredients in Testim® are purified water, pentadecalactone, carbopol, acrylates, propylene glycol, glycerin, polyethylene glycol, ethanol (74%), and tromethamine.

CLINICAL PHARMACOLOGY

Testim® 1% (testosterone gel) delivers physiologic amounts of testosterone, producing circulating testosterone levels that approximate normal levels (e.g., 300 – 1000 ng/dL) seen in healthy men.

Testosterone – General Androgen Effects:

Testosterone and dihydrotestosterone (DHT), endogenous androgens, are responsible for normal growth and development of the male sex organs and for maintenance of secondary sex characteristics. These effects include the growth and maturation of the prostate, seminal vesicles, penis, and scrotum; the development of male hair distribution, such as facial, pubic, chest, and axillary hair; laryngeal enlargement; vocal cord thickening; alterations in body musculature; and fat distribution.

Male hypogonadism results from insufficient secretion of testosterone and is characterized by low serum testosterone concentrations. Symptoms associated with male hypogonadism include decreased sexual desire with or without impotence, fatigue and loss of energy, mood depression, regression of secondary sexual characteristics, and osteoporosis. Hypogonadism is a risk factor for osteoporosis in men.

Drugs in the androgen class also promote retention of nitrogen, sodium, potassium, phosphorus, and decreased urinary excretion of calcium.

Androgens have been reported to increase protein anabolism and decrease protein catabolism. Nitrogen balance is improved only when there is sufficient intake of calories and protein. Androgens have been reported to stimulate the production of red blood cells by enhancing erythropoietin production.

Androgens are responsible for the growth spurt of adolescence and for the eventual termination of linear growth brought about by fusion of the epiphyseal growth centers. In children, exogenous androgens accelerate linear growth rates but may cause a disproportionate advancement in bone maturation. Use over long periods may result in fusion of the epiphyseal growth centers and termination of the growth process.

During exogenous administration of androgens, endogenous testosterone release may be inhibited through feedback inhibition of pituitary luteinizing hormone (LH). At large doses of exogenous androgens, spermatogenesis may also be suppressed through feedback inhibition of pituitary follicle-stimulating hormone (FSH).

There is a lack of substantial evidence that androgens are effective in accelerating fracture healing or in shortening post-surgical convalescence.

Pharmacokinetics

The pharmacokinetics of Testim® have been evaluated with administration of doses containing 50 mg and 100 mg of testosterone to adult males with morning testosterone levels ≤300 ng/dL.

Absorption
Testim® is a topical formulation that dries quickly when applied to the skin surface. The skin serves as a reservoir for the sustained release of testosterone into the systemic circulation. Approximately 10% of the testosterone applied on the skin surface is absorbed into the systemic circulation during a 24-hour period.

Single Dose
In single dose studies, when either Testim® 50 mg or 100 mg was administered, absorption of testosterone into the blood continued for the entire 24 hour dosing period. Also, mean peak and average serum concentrations within the normal range were achieved within 24 hours.

Multiple Dose
With single daily applications of Testim® 50 mg and 100 mg, follow-up measurements at 30 and 90 days after starting treatment have confirmed that serum testosterone and DHT concentrations are generally maintained within the normal range.

Figure 1 summarizes the 24-hour pharmacokinetic profile of testosterone for patients maintained on Testim® 50 mg or Testim® 100 mg for 30 days.

Figure 1
Mean Steady-State Serum Testosterone (±SD) (ng/dL) Concentrations on Day 30 in Patients Applying Testim® Once Daily

The average daily testosterone concentration produced by Testim® 100 mg at Day 30 was 612 (± 286) ng/dL and by Testim® 50 mg at Day 30 was 365 (± 187) ng/dL.

Figure 2 summarizes the 24-hour pharmacokinetic profile of DHT for patients maintained on Testim® 50 mg or Testim® 100 mg for 30 days.

Figure 2
Mean Steady-State Serum Dihydrotestosterone (±SD) (pg/mL) Concentrations on Day 30 in Patients Applying Testim® Once Daily

The average daily DHT concentration produced by Testim® 100 mg at Day 30 was 555 (± 293) pg/mL and by Testim® 50 mg at Day 30 was 346 (± 212) pg/mL.

Washing
The effect of showering (with mild soap) at 1, 2 and 6 hours post application of Testim® 100 mg was evaluated in a clinical trial in 12 men. The study demonstrated that the overall effect of washing was to lessen testosterone levels; however, when washing occurred two or more hours post drug application, serum testosterone levels remained within the normal range.

Distribution

Circulating testosterone is chiefly bound in the serum to sex hormone-binding globulin (SHBG) and albumin. The albumin-bound fraction of testosterone easily dissociates from albumin and is presumed to be bioactive. The portion of testosterone bound to SHBG is not considered biologically active. Approximately 40% of testosterone in plasma is bound to SHBG, 2% remains unbound (free) and the rest is bound to albumin and other proteins. The amount of SHBG in the serum and the total testosterone level will determine the distribution of bioactive and nonbioactive androgen.

Metabolism

There is considerable variation in the half-life of testosterone as reported in the literature, ranging from ten to 100 minutes.

Testosterone is metabolized to various 17-keto steroids through two different pathways. The major active metabolites of testosterone are estradiol and DHT. Testosterone is metabolized to DHT by steroid 5α-reductase located in the skin, liver, and the urogenital tract of the male. DHT binds with greater affinity to SHBG than does testosterone. In many tissues, the activity of testosterone depends on its reduction to DHT, which binds to cytosol receptor proteins. The steroid-receptor complex is transported to the nucleus where it initiates transcription and cellular changes related to androgen action. In reproductive tissues, DHT is further metabolized to 3α and 3β androstanediol. Inactivation of testosterone occurs primarily in the liver.

DHT concentrations increased in parallel with testosterone concentrations during Testim® treatment. After 90 days of treatment, mean DHT concentrations remained generally within the normal range for Testim®-treated subjects.

Excretion

About 90% of a testosterone dose given intramuscularly is excreted in the urine as glucuronic and sulfuric acid conjugates of testosterone and metabolites; about 6% of a dose is excreted in the feces, mostly in the unconjugated form.

Special Population

In patients treated with Testim® there are no observed differences in the average daily serum testosterone concentration at steady-state based on age or cause of hypogonadism. No formal studies were conducted in a pediatric age population or in patients with renal or hepatic insufficiencies.

Clinical Studies

Testim® was evaluated in a randomized multicenter, multi-dose, active and placebo controlled 90-day study in 406 adult males with morning testosterone levels ≤300 ng/dL. The study was double-blind for the doses of Testim® and placebo, but open label for the non-scrotal testosterone transdermal system. During the first 60 days, patients were evenly randomized to Testim® 50 mg, Testim® 100 mg, placebo gel, or testosterone transdermal system. At Day 60, patients receiving Testim® were maintained at the same dose, or were titrated up or down within their treatment group, based on 24-hour averaged serum testosterone concentration levels obtained on Day 30.

Of 192 hypogonadal men who were appropriately titrated with Testim® and who had sufficient data for analysis, 74% achieved an average serum testosterone level within the normal range on treatment Day 90.

Table 1 summarizes the mean testosterone concentrations on Day 30 for patients receiving Testim® 50 mg or 100 mg.

Table 1: Mean (± SD) Steady-State Serum Testosterone Concentrations on Day 30
 | Testim® 50 mg n=94 | Testim® 100 mg n=95 | Placebo n=93
Cavg (ng/dL) | 365 ± 187 | 612 ± 286 | 216 ± 79
Cmax (ng/dL) | 538 ± 371 | 897 ± 565 | 271 ± 110
Cmin (ng/dL) | 223 ± 126 | 394 ±189 | 164 ± 64

At Day 30, patients receiving Testim® 100 mg daily showed significant improvement from baseline in multiple sexual function parameters as measured by patient questionnaires when compared to placebo. These parameters included sexual motivation, sexual desire, sexual activity and spontaneous erections. For Testim® 100 mg, improvements in sexual motivation, spontaneous erections, and sexual desire were maintained through Day 90. Sexual enjoyment and satisfaction with erection duration were improved compared to baseline but these improvements were not significant compared to the placebo group.

In Testim®-treated patients, the number of days in which sexual activity was reported to occur increased by 123% from baseline at Day 30 and was still increased from baseline by 59% at Day 90. The number of days with spontaneous erections increased by 137% at Day 30 and was maintained at 78% at Day 90 for Testim®-treated patients compared to baseline.

Table 2 summarizes the changes in body composition at Day 90 for patients receiving Testim® 50 mg or 100 mg as measured by standardized whole body DEXA (Dual Energy X-ray Absorptiometry) scanning.

Table 2: Effect of Testim® on Lean Body Mass, Total Fat Mass and % Body Fat
Days of Treatment | Lean Body Mass (Muscle) (kg) | Total Fat Mass (kg) | % Body Fat
Baseline | 61.6 | 29.4 | 30.9
Day 90 | 63.3 | 28.6 | 29.8
Change from Baseline | ↑1.6 | ↓0.8 | ↓1.1

At Day 90, mean increases from baseline in lean body mass and mean decreases from baseline in total fat mass and percent body fat in Testim®-treated patients were significant when compared to placebo-treated patients.

Potential for Testosterone Transfer
The potential for dermal testosterone transfer following Testim® use was evaluated in two clinical trials with males dosed with Testim® and their untreated female partners.

In the first trial (AUX-TG-206), 30 couples were evenly randomized to five groups. In the first four groups, 100 mg of Testim® was applied to the male abdomen and the couples were then asked to rub abdomen-to-abdomen for 15 minutes at 1 hour, 4 hours, 8 hours or 12 hours after dose application, respectively. In these couples, serum testosterone concentrations in female partners increased from baseline by at least 4 times and potential for transfer was seen at all timepoints.

When 6 males used a shirt to cover the abdomen at 15 minutes post-application and partners again rubbed abdomens for 15 minutes at the 1 hour timepoint, the potential for transfer was markedly reduced.

In the second trial (AUX-TG-209), 24 couples were evenly randomized to four groups. Testim® 100 mg was applied to the male arms and shoulders. In one group, 15 minutes of direct skin-to-skin rubbing began at 4 hours after application. In these six women, all of whom showered immediately after the rubbing activity, mean maximum serum testosterone concentrations increased from baseline by approximately 4 times. When males wore a long-sleeved T-shirt and rubbing was started at 1 and at 4 hours after application, the transfer of testosterone from male to female partners was prevented.

INDICATIONS AND USAGE

Testim® is indicated for testosterone replacement therapy in adult males for conditions associated with a deficiency or absence of endogenous testosterone:

1. Primary hypogonadism (congenital or acquired): testicular failure due to cryptorchidism, bilateral torsion, orchitis, vanishing testis syndrome, orchiectomy, Klinefelter's syndrome, chemotherapy, or toxic damage from alcohol or heavy metals. These men usually have low serum testosterone levels and gonadotropins (FSH, LH) above the normal range.
2. Hypogonadotropic hypogonadism (congenital or acquired): idiopathic gonadotropin or luteinizing hormone-releasing hormone (LHRH) deficiency or pituitary-hypothalamic injury from tumors, trauma, or radiation. These men have low testosterone serum levels but have gonadotropins in the normal or low range.

Testim® has not been clinically evaluated in males under 18 years of age.

CONTRAINDICATIONS

Androgens are contraindicated in men with carcinoma of the breast or known or suspected carcinoma of the prostate. Testim® is not indicated for use in women, has not been evaluated for use in women, and must not be used in women.

Pregnant and nursing women should avoid skin contact with Testim® application sites on men. Testosterone may cause fetal harm. Testosterone exposure during pregnancy has been reported to be associated with fetal abnormalities. In the event that unwashed or unclothed skin to which Testim® has been applied comes in direct contact with the skin of a pregnant or nursing woman, the general area of contact on the woman should be immediately washed with soap and water.

Testim® should not be used in patients with known hypersensitivity to any of its ingredients, including testosterone USP that is chemically synthesized from soy.

WARNINGS

1. Men with benign prostatic hyperplasia (BPH) are at an increased risk for worsening of BPH. In addition, men treated with androgens may be at an increased risk for prostate cancer. Geriatric patients and other patients with clinical or demographic characteristics that are recognized to be associated with an increased risk of prostate cancer should be evaluated for the presence of prostate cancer prior to initiation of testosterone replacement therapy. In men receiving testosterone replacement therapy, surveillance for prostate cancer should be consistent with current practices for eugonadal men (see PRECAUTIONS, Carcinogenesis, Mutagenesis, Impairment of Fertility and Laboratory Tests).
2. Potential for Secondary Exposure to Testosterone
  - Secondary exposure to testosterone in children and women can occur with testosterone gel use in men. Cases of secondary exposure resulting in virilization of children have been reported in postmarketing surveillance of testosterone-containing gel products. Signs and symptoms have included enlargement of the penis or clitoris, development of pubic hair, increased erections and libido, aggressive behavior, and advanced bone age. In most cases, these signs and symptoms regressed with removal of the exposure to testosterone. In a few cases, however, enlarged genitalia did not fully return to age-appropriate normal size, and bone age remained modestly greater than chronological age. The risk of transfer was increased in some of these cases by not adhering to precautions for the appropriate use of the testosterone gel product.
  - Inappropriate changes in genital size or development of pubic hair or libido in children, or changes in body hair distribution, significant increase in acne, or other signs of virilization in adult women should be brought to the attention of a physician, and the possibility of secondary exposure to testosterone gel should also be brought to the attention of a physician. Testosterone gel should be promptly discontinued until the cause of virilization has been identified.
3. Strict adherence to the following precautions is advised in order to minimize the potential for secondary exposure to testosterone from Testim®-treated skin:
  - Children and women should avoid contact with Testim® application sites on the skin of men using Testim.
  - Testim® should only be applied to the shoulders or upper arms (area of application should be limited to the area that will be covered by the patient’s short sleeve t-shirt).
  - Patients should wash their hands thoroughly and immediately with soap and water after application of Testim®.
  - Patients should cover the application site(s) with clothing (e.g., a shirt) after the gel has dried.
  - Prior to any situation in which skin-to-skin contact is anticipated, patients should wash the application site(s) thoroughly with soap and water to remove any testosterone residue.
  - In the event that unwashed or unclothed skin to which Testim® has been applied comes in direct contact with the skin of another person, the general area of contact on the other person should be washed with soap and water as soon as possible. Studies show that residual testosterone is removed from the skin surface by washing with soap and water.
4. Testim® should not be applied to the abdomen.
5. Prolonged use of high doses of orally active 17-alpha-alkyl androgens (e.g., methyltestosterone) has been associated with serious hepatic adverse effects (peliosis hepatis, hepatic neoplasms, cholestatic hepatitis, and jaundice). Peliosis hepatis can be a life-threatening or fatal complication. Long-term therapy with testosterone enanthate, which elevates blood levels for prolonged periods has produced multiple hepatic adenomas. Transdermal testosterone is not known to produce these adverse effects.
6. Edema, with or without congestive heart failure, may be a serious complication in patients with preexisting cardiac, renal, or hepatic disease. In addition to discontinuation of the drug, diuretic therapy may be required.
7. Gynecomastia occasionally develops and occasionally persists in patients being treated for hypogonadism.
8. The treatment of hypogonadal men with testosterone may potentiate sleep apnea in some patients, especially those with risk factors such as obesity or chronic lung diseases.

PRECAUTIONS

General

The physician should instruct patients to report any of the following:

- Too frequent or persistent erections of the penis.
- Any changes in skin color, ankle swelling or unexplained nausea and vomiting.
- Breathing disturbances, including those associated with sleep.

Information for Patients

Advise patients to carefully read the Medication Guide that accompanies each carton of Testim® single-use tubes.

Advise patients of the following:

1. Men with known or suspected prostate or breast cancer should not use Testim®.
2. Secondary exposure to testosterone in children and women can occur with the use of testosterone gel products in men. Cases of secondary exposure to testosterone have been reported in children with signs and symptoms including enlargement of the penis or clitoris, premature development of pubic hair, increased erections, and aggressive behavior.
  Unexpected sexual development including inappropriate enlargement of the penis or clitoris, premature development of pubic hair, increased erections, and aggressive behavior in children, or changes in hair distribution, increase in acne, or other signs of testosterone effects in adult women should be brought to the attention of a physician and the possibility of secondary exposure to testosterone gel also should be brought to the attention of a physician. Testosterone gel should be promptly discontinued until the cause of virilization is identified.
3. Strict adherence to the following precautions is advised in order to minimize the potential for secondary exposure to testosterone from Testim®-treated skin:
  - Children and women should avoid contact with Testim® application sites on the skin of men using Testim®.
  - Testim® should only be applied to the shoulders or upper arms (area of application should be limited to the area that will be covered by the patient’s short sleeve t-shirt).
  - Patients should wash their hands thoroughly and immediately with soap and water after application of Testim®.
  - Patients should cover the application site(s) with clothing (e.g., a shirt) after the gel has dried.
  - Prior to any situation in which skin-to-skin contact is anticipated, patients should wash the application site(s) thoroughly with soap and water to remove any testosterone residue.
  - In the event that unwashed or unclothed skin to which testosterone gel has been applied comes in direct contact with the skin of another person, the general area of contact on the other person should be washed with soap and water as soon as possible. Studies show that residual testosterone is removed from the skin surface by washing with soap and water.

Also advise patients of the following:

- Testim® should not be applied to the scrotum, penis, or abdomen.
- Testim® should be applied once daily at approximately the same time each day to clean dry skin of the shoulders and/or upper arms.
- Washing or swimming may lessen testosterone levels; however, when washing occurs two or more hours post drug application, serum testosterone levels remain within the normal range.

Laboratory Tests

1. Hemoglobin and hematocrit levels should be checked periodically (to detect polycythemia) in patients on long-term androgen therapy.
2. Liver function, prostate specific antigen (PSA), cholesterol, and high-density lipoprotein (HDL) should be checked periodically.
3. To ensure proper dosing, serum testosterone concentrations should be measured (see DOSAGE AND ADMINISTRATION).

Drug Interactions

Oxyphenbutazone: Concurrent administration of oxyphenbutazone and androgens may result in elevated serum levels of oxyphenbutazone.

Insulin: In diabetic patients, the metabolic effects of androgens may decrease blood glucose and, therefore, insulin requirements.

Propranolol: In a published pharmacokinetic study of an injectable testosterone product, administration of testosterone cypionate led to an increased clearance of propranolol in the majority of men tested. It is unknown if this would apply to Testim®.

Corticosteroids: The concurrent administration of testosterone with ACTH or corticosteroids may enhance edema formation; thus these drugs should be administered cautiously, particularly in patients with cardiac or hepatic disease.

Drug/Laboratory Test Interactions

Androgens may decrease levels of thyroxin-binding globulin, resulting in decreased total T4 serum levels and increased resin uptake of T3 and T4. Free thyroid hormone levels remain unchanged, however, and there is no clinical evidence of thyroid dysfunction.

Carcinogenesis, Mutagenesis, Impairment of Fertility

Animal Data: Testosterone has been tested by subcutaneous injection and implantation in mice and rats. In mice, the implant induced cervical-uterine tumors, which metastasized in some cases. There is suggestive evidence that injection of testosterone into some strains of female mice increases their susceptibility to hepatoma. Testosterone is also known to increase the number of tumors and decrease the degree of differentiation of chemically induced carcinomas of the liver in rats.

Human Data: There are rare reports of hepatocellular carcinoma in patients receiving long-term oral therapy with androgens in high doses. Withdrawal of the drugs did not lead to regression of the tumors in all cases.

Geriatric patients treated with androgens may be at an increased risk for the development of prostatic hyperplasia and prostatic carcinoma. Geriatric patients and other patients with clinical or demographic characteristics that are recognized to be associated with an increased risk of prostate cancer should be evaluated for the presence of prostate cancer prior to initiation of testosterone replacement therapy.

In men receiving testosterone replacement therapy, surveillance for prostate cancer should be consistent with current practices for eugonadal men.

PREGNANCY

Pregnancy Category X (see Contraindications) – Teratogenic Effects: Testim® is not indicated for women and must not be used in women. Testosterone may cause fetal harm.

NURSING MOTHERS

Nursing Mothers: Testim® is not indicated for women and must not be used in nursing mothers.

PEDIATRIC USE

Pediatric Use: Safety and efficacy of Testim® in patients <18 years old has not been established.

ADVERSE REACTIONS

In a controlled clinical study, 304 patients were treated with Testim® 50 mg or 100 mg or placebo gel for up to 90 days. Two hundred-five (205) patients received Testim® 50 mg or 100 mg daily and 99 patients received placebo. Patients with adverse events that were possibly or probably related to study drug and reported by ≥1% of the Testim® patients and greater than placebo are listed in Table 3.

Table 3: Incidence of Adverse Events Judged Possibly, Probably or Definitely Related to Use of Testim® in the Controlled Clinical Trial
Event | Testim® 50 mg | Testim® 100 mg | Placebo
Application Site Reactions | 2% | 4% | 3%
Benign Prostatic Hyperplasia | 0% | 1% | 1%
Blood Pressure Diastolic Decreased | 1% | 0% | 0%
Blood Pressure Increased | 1% | 1% | 0%
Gynecomastia | 1% | 0% | 0%
Headache | 1% | 1% | 0%
Hematocrit/hemoglobin Increased | 1% | 2% | 0%
Hot Flushes | 1% | 0% | 0%
Insomnia | 1% | 0% | 0%
Lacrimation Increased | 1% | 0% | 0%
Mood Swings | 1% | 0% | 0%
Smell Disorder | 1% | 0% | 0%
Spontaneous Penile Erection | 1% | 0% | 0%
Taste Disorder | 1% | 1% | 0%

The following adverse events possibly or probably related to Testim® occurred in fewer than 1% of patients but were greater in Testim® groups compared to the placebo group: activated partial thromboplastin time prolonged, blood creatinine increased, prothrombin time prolonged, appetite increased, sensitive nipples, and acne.

In this clinical trial of Testim®, six patients had adverse events that led to their discontinuation. These events included: vertigo, coronary artery disease, depression with suicidal ideation, urinary tract infection/pneumonia (none of which were considered related to Testim® administration), mood swings and hypertension. No Testim® patients discontinued due to skin reaction.

In one foreign Phase 3 trial, one subject discontinued due to a skin-related adverse event. In the pivotal U.S. and European Phase 3 trials combined, at the 50 mg dosage strength, the percentage of subjects reporting clinically notable increases in hematocrit or hemoglobin were similar to placebo. However, in the 100 mg dose group, 2.3% and 2.8% of patients had a clinically notable increase in hemoglobin (≥ 19 gm/dL) or hematocrit (≥ 58%), respectively.

In the combined ongoing U.S. and European open label extension studies, approximately 140 patients received Testim® for at least 6 months. The preliminary results from these studies are consistent with those reported for the U.S. controlled clinical trial.

Postmarketing Experience

The following adverse reactions have been identified during post-approval use of testosterone gel products. Because the reactions are reported voluntarily from a population of uncertain size, it is not always possible to reliably estimate their frequency or establish a causal relationship to drug exposure.

Secondary Exposure to Testosterone in Children

Cases of secondary exposure to testosterone resulting in virilization of children have been reported in postmarketing surveillance of testosterone gel products. Signs and symptoms of these reported cases have included enlargement of the clitoris (with surgical intervention) or of the penis, development of pubic hair, increased erections and libido, aggressive behavior, and advanced bone age. In most cases with a reported outcome, these signs and symptoms were reported to have regressed with removal of the testosterone gel exposure. In a few cases, however, enlarged genitalia did not fully return to age-appropriate normal size, and bone age remained modestly greater than chronological age. In some of the cases, direct contact with the sites of application on the skin of men using testosterone gel was reported. In at least one reported case, the reporter considered the possibility of secondary exposure from items such as the testosterone gel user’s shirts and/or other fabrics, such as towels and sheets (see WARNINGS).

DRUG ABUSE AND DEPENDENCE

Testim® contains testosterone, a Schedule III controlled substance as defined by the Anabolic Steroids Control Act. Oral ingestion of Testim® will not result in clinically significant serum testosterone concentrations due to extensive first-pass metabolism.

OVERDOSAGE

There were no reports of overdose in the Testim® clinical trials. There is one report of acute overdosage by injection of testosterone enanthate: testosterone levels of up to 11,400 ng/dL were implicated in a cerebrovascular accident.

DOSAGE AND ADMINISTRATION

The recommended starting dose of Testim® is 5 g of gel (one tube) containing 50 mg of testosterone applied once daily (preferably in the morning) to clean, dry intact skin of the shoulders and/or upper arms (area of application should be limited to the area that will be covered by the patient’s short sleeve t-shirt). Morning serum testosterone levels should then be measured approximately 14 days after initiation of therapy to ensure proper serum testosterone levels are achieved. If the serum testosterone concentration is below the normal range, or if the desired clinical response is not achieved, the daily Testim® dose may be increased from 5 g (one tube) to 10 g (two tubes) as instructed by the physician.

Upon opening the tube the entire contents should be squeezed into the palm of the hand and immediately applied to the shoulders and/or upper arms (area of application should be limited to the area that will be covered by the patient’s short sleeve t-shirt). Application sites should be allowed to dry for a few minutes prior to dressing. Hands should be washed thoroughly with soap and water after Testim® has been applied.

In order to prevent transfer to another person, clothing should be worn to cover the application sites. If direct skin-to-skin contact with another person is anticipated, the application sites must be washed thoroughly with soap and water.

In order to maintain serum testosterone levels in the normal range, the sites of application should not be washed for at least two hours after application of Testim®.

Do not apply Testim® to the genitals or to the abdomen.

HOW SUPPLIED

Testim® contains testosterone, a Schedule III controlled substance as defined by the Anabolic Steroids Control Act. Testim® is supplied in unit-dose tubes in cartons of 30. Each tube contains 50 mg testosterone in 5 g of gel, and is supplied as follows:

NDC Number | Strength | Package Size
54868-4989-0 | 1% (50 mg) | 30 tubes: 5 g per tube

Storage

Store at room temperature 25°C (77°F); Excursions permitted to 15°-30°C (59°-86°F) [See USP Controlled Room Temperature].

Disposal
Keep out of the reach of children.
Used Testim® tubes should be discarded in household trash in a manner that prevents accidental exposure of children or pets; contents flammable.

RX Only

Manufactured for:
Auxilium Pharmaceuticals, Inc.
Malvern, PA 19355 USA
By: DPT Laboratories, Ltd.
San Antonio, TX 78215

Issued: September 2009
PL-0705-001.b
129092

Additional barcode labeling by:
Physicians Total Care, Inc.
Tulsa, Oklahoma 74146

Medication Guide

TESTIM® (těs TIM) 1%, CIII
(testosterone gel)

Read the Medication Guide that comes with TESTIM before you start taking it and each time you get a refill. There may be new information. This Medication Guide does not take the place of talking to your doctor about your medical condition or your treatment.

What is the most important information I should know about TESTIM?

1. Early signs and symptoms of puberty have happened in young children who were accidentally exposed to testosterone through contact with men using TESTIM.
  Signs and symptoms of early puberty in a child may include:
  - enlarged penis or clitoris
  - early development of pubic hair
  - increased erections or sex drive
  - aggressive behavior
2. TESTIM can transfer from your body to others. Women and children should avoid contact with the unwashed or unclothed area where TESTIM has been applied to your skin.
  Stop using TESTIM and call your doctor right away if you see any signs and symptoms in a child or a woman that may have occurred through accidental exposure to TESTIM.
  Signs and symptoms of exposure to Testim in children may include:
  - enlarged penis or clitoris
  - early development of pubic hair
  - increased erections or sex drive
  - aggressive behavior
  Signs and symptoms of exposure to TESTIM in women may include:
  - changes in body hair
  - a large increase in acne

To lower the risk of transfer of TESTIM from your body to others, you should follow these important instructions:

- Apply TESTIM only to the areas of your shoulders and upper arms that will be covered by a short sleeve T-shirt.
- Wash your hands right away with soap and water after applying TESTIM.
- After the gel has dried, cover the application area with clothing. Keep the area covered until you have washed the application area well or have showered.
- If you expect to have skin-to-skin contact with another person, first wash the application area well with soap and water.
- If a woman or child makes contact with the TESTIM application area, that area on the woman or child should be washed well with soap and water right away.

What is TESTIM?

TESTIM is a prescription medicine that contains testosterone. TESTIM is used to treat adult males who have low or no testosterone.

It is not known if TESTIM is safe or effective in children younger than 18 years old. Exposure of children to testosterone may affect bone growth.

TESTIM is a controlled substance (CIII) because it contains testosterone that can be a target for people who abuse prescription medicines. Keep your TESTIM in a safe place to protect it. Never give your TESTIM to anyone else, even if they have the same symptoms you have. Selling or giving away this medicine may harm others and it is against the law.

Who should not use TESTIM?

TESTIM is not meant for use in women.

Do not use TESTIM if you:

- have breast cancer
- have or might have prostate cancer
- are pregnant or may become pregnant or are breast-feeding. TESTIM may harm your unborn or breast-feeding baby.
  Women who are pregnant or who may become pregnant should avoid contact with the area of skin where TESTIM has been applied.
- are allergic to testosterone or any of the ingredients in TESTIM including soy. See the end of this Medication Guide for a complete list of ingredients in TESTIM.

Talk to your doctor before taking this medicine if you have any of the above conditions.

What should I tell my doctor before using TESTIM?
Before you use TESTIM, tell your doctor if you:

- have breast cancer or prostate cancer
- have urinary problems due to an enlarged prostate
- have heart problems
- have liver or kidney problems
- have problems breathing while you sleep (sleep apnea)
- have any other medical conditions

Tell your doctor about all the medicines you take, including prescription and non-prescription medicines, vitamins, and herbal supplements.
TESTIM and certain other medicines you take can affect each other.

Especially, tell your doctor if you take:

- insulin
- propranolol
- corticosteroids

Ask your doctor or pharmacist for a list of these medicines, if you are not sure.
Know the medicines you take. Keep a list of them and show it to your doctor and pharmacist when you get a new medicine.

How should I use TESTIM?

- It is important that you apply TESTIM exactly as prescribed by your doctor. Your doctor will tell you how much TESTIM to apply and when to apply it.
- Your doctor may change your TESTIM dose. Do not change your TESTIM dose without talking to your doctor.
- Your doctor will test your blood before you start and while you take TESTIM.
- TESTIM is for skin use only.
- Apply TESTIM only to the areas of your shoulders and upper arms that will be covered by a short sleeve t-shirt. Apply TESTIM at the same time each day.
- Do not apply TESTIM to your penis, scrotum or abdomen.

To apply TESTIM:

- Remove the cap from the tube and use the top of the cap to pierce the metal seal on the top of the tube.
- Squeeze all of the TESTIM out of the tube into the palm of your hand. Squeeze from the bottom of the tube to the top.
- Apply all of the TESTIM gel to your shoulders and upper arms. Rub the gel onto your skin for several seconds until the gel is dry.
- Replace the cap and throw away the tube in the trash out of the reach of children to avoid accidental exposure.
- Wash you hands with soap and water right away after you apply TESTIM.
- Let the application areas dry for a few minutes before putting on a shirt.
- To reduce transfer of TESTIM to others, clothes (such as a t-shirt) should always be worn to cover the TESTIM application areas until you have washed the application areas well with soap and water.
- Wait at least 2 hours after applying TESTIM before showering or swimming to make sure TESTIM is absorbed into your body.
- TESTIM is flammable until dry. Let the gel dry before smoking or going near an open flame.

What are the possible side effects of TESTIM?

TESTIM can cause serious side effects including:

- See “What is the most important information I should know about TESTIM?”.
- If you already have enlargement of your prostate gland your signs and symptoms can get worse while using TESTIM. This can include:
  - increased urination at night
  - trouble starting your urine stream
  - having to pass urine many times during the day
  - having an urge that you have to go to the bathroom right away
  - having a urine accident
  - being unable to pass urine or weak urine flow
- Possible increased risk of prostate cancer. Your doctor should check you for prostate cancer or any other prostate problems before you start and while you use TESTIM.
- In large doses TESTIM may lower your sperm count.
- Swelling of your ankles, feet, or body, with or without heart failure. This may cause serious problems for people who have heart, kidney or liver disease.
- Enlarged or painful breasts.
- Having problems breathing while you sleep (sleep apnea).
- Blood clots in the legs. This can include pain, swelling or redness of your legs.

Call your doctor right away if you have any of the serious side effects listed above.

The most common side effects of TESTIM include:

- skin irritation where TESTIM is applied
- increased red blood cell count
- headache
- increased blood pressure

Other side effects include more erections than are normal for you or erections that last a long time.

Tell your doctor if you have any side effect that bothers you or that does not go away.
These are not all the possible side effects of TESTIM. For more information, ask your doctor or pharmacist.
Call your doctor for medical advice about side effects. You may report side effects to FDA at 1-800-FDA-1088.

How should I store TESTIM?

- Store TESTIM between 59°F to 86°F (15°C to 30°C).
- Safely throw away used TESTIM tubes in household trash. Be careful to prevent accidental exposure of children or pets.
- Keep TESTIM away from fire.

Keep TESTIM and all medicines out of the reach of children.

General information about TESTIM

Medicines are sometimes prescribed for purposes other than those listed in a Medication Guide. Do not use TESTIM for a condition for which it was not prescribed. Do not give TESTIM to other people, even if they have the same symptoms that you have. It may harm them.
This Medication Guide summarizes the most important information about TESTIM. If you would like more information, talk with your doctor. You can ask your pharmacist or doctor for information about TESTIM that is written for health professionals.
For more information, go to www.TESTIM.com or call 1-877-663-0412.

What are the ingredients in TESTIM?

Active ingredient: testosterone (that may be made from soy)

Inactive ingredients: purified water, pentadecalactone, carbopol, acrylates, propylene glycol, glycerin, polyethylene glycol, ethanol (74%), and tromethamine.

This Medication Guide has been approved by the US Food and Drug Administration.
Manufactured for:
Auxilium Pharmaceuticals, Inc.
Malvern, PA 19355 USA
By: DPT Laboratories, Ltd.
San Antonio, TX 78215
Medication Guide issued: 11/2011
PL-0705-002.c
129794

PACKAGE LABEL

Package Label - Principal Display Panel – 5 g Tube Label